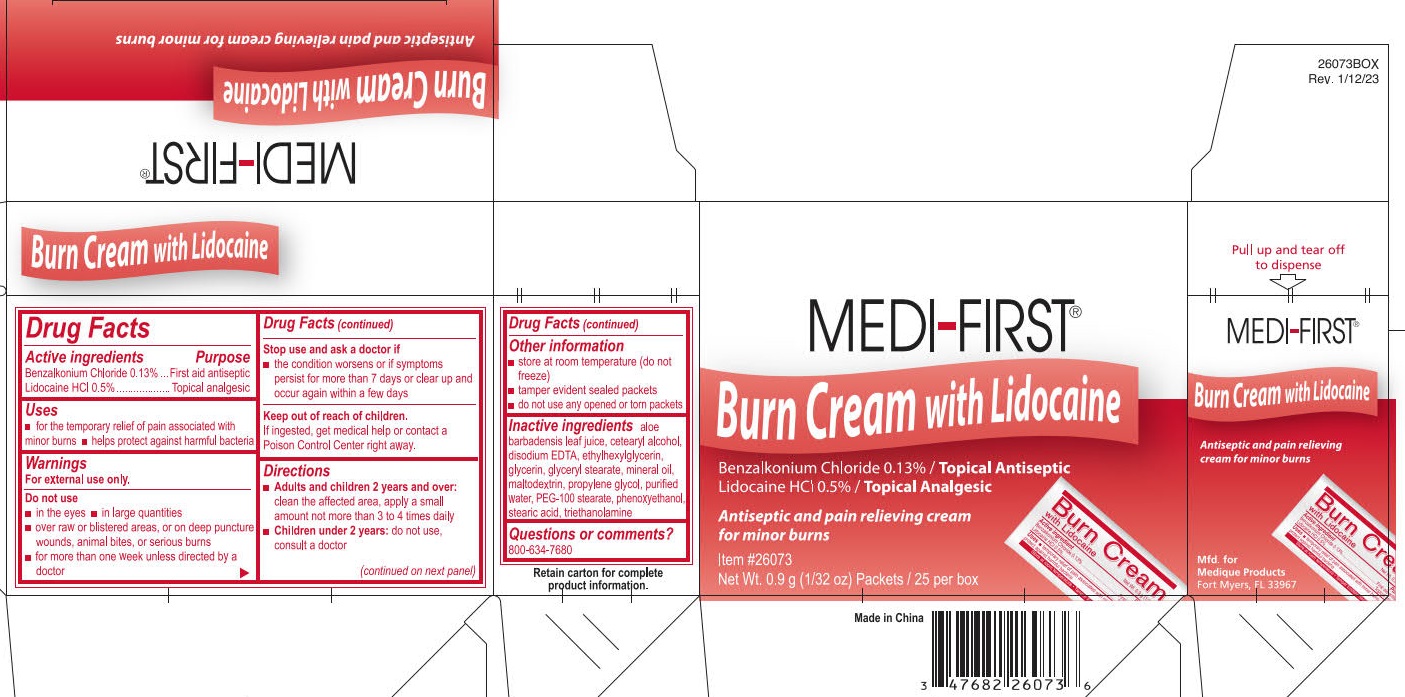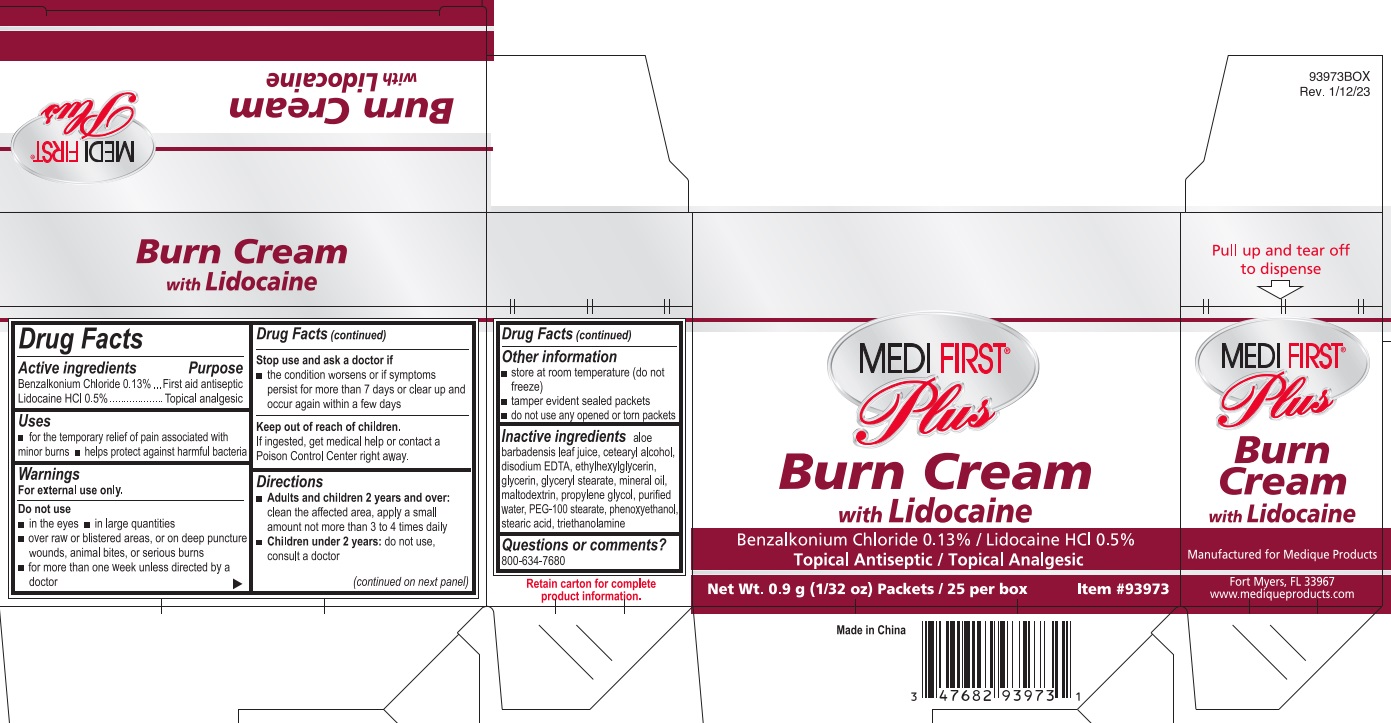 DRUG LABEL: Medi-First Plus Burn with Lidocaine
NDC: 47682-985 | Form: CREAM
Manufacturer: Unifirst First Aid Corporation
Category: otc | Type: HUMAN OTC DRUG LABEL
Date: 20250909

ACTIVE INGREDIENTS: BENZALKONIUM CHLORIDE 1.3 mg/1 g; LIDOCAINE HYDROCHLORIDE 5 mg/1 g
INACTIVE INGREDIENTS: PROPYLENE GLYCOL; ETHYLHEXYLGLYCERIN; GLYCERIN; MALTODEXTRIN; PHENOXYETHANOL; WATER; PEG-100 STEARATE; CETOSTEARYL ALCOHOL; TROLAMINE; ALOE VERA LEAF; GLYCERYL STEARATE SE; MINERAL OIL; EDETATE DISODIUM

Medi-First Burn Cream with Lidocaine

Drug Facts

Active ingredients

Benzalkonium Chloride 0.13%

Lidocaine HCl 0.5%

Purpose

First aid antiseptic

Topical analgesic

Uses

- for the temporary relief of pain associated with minor burns
- helps protect against harmful bacteria

Warnings

For external use only.

Do not use

- in the eyes
- in large quantities
- over raw or blistered areas, or on deep puncture wounds, aniaml bites, or serious burns
- for more than one week unless directed by a doctor

Stop use and ask a doctor if

- the condition worsens or if symptoms persist for more than 7 days or clear up and occur again within a few days

Keep out of reach of children.

If ingested, get medical help or contact a Poison Control Center right away.

Directions

- Adults and children 2 years and over: clean the affected area, apply a small amount not more than 3 to 4 times daily
- Children under 2 years: do not use, consult a doctor

Other information

- store at room temperature (do not freeze)
- tamper evident sealed packets
- do not use any opened or torn packets

Inactive ingredients

aloe barbadensis leaf juice, cetearyl alcohol, disodium EDTA, ethylhexlglycerin, glycerin, glyceryl stearate, mineral oil, maltodextrin, propylene glycol, purified water, PEG-100 stearate, phenoxyethanol, stearic acid, triethanolamine

Questions or comments? 800-634-7680

PACKAGE LABEL

Medi-First®

Burn Cream with Lidocaine

Benzalkonium Chloride 0.13% / Topical Antiseptic

Lidocaine HCl 0,5% / Topical Analgesic

Antiseptic and pain relieving cream for minor burns

Item #26073

NetWt. 0.9 g (1/32 oz) Packets / 25 per box

Made in China

PACKAGE LABEL

Medi-First® Plus

Burn Cream with Lidocaine

Benzalkonium Chloride 0.13% / Lidocaine HCl 0.5%

Topical Antiseptic / Topical Analgesic

Net Wt. 0.9 g (1/32 oz) Packets / 25 per box

Item #93973

Made in China